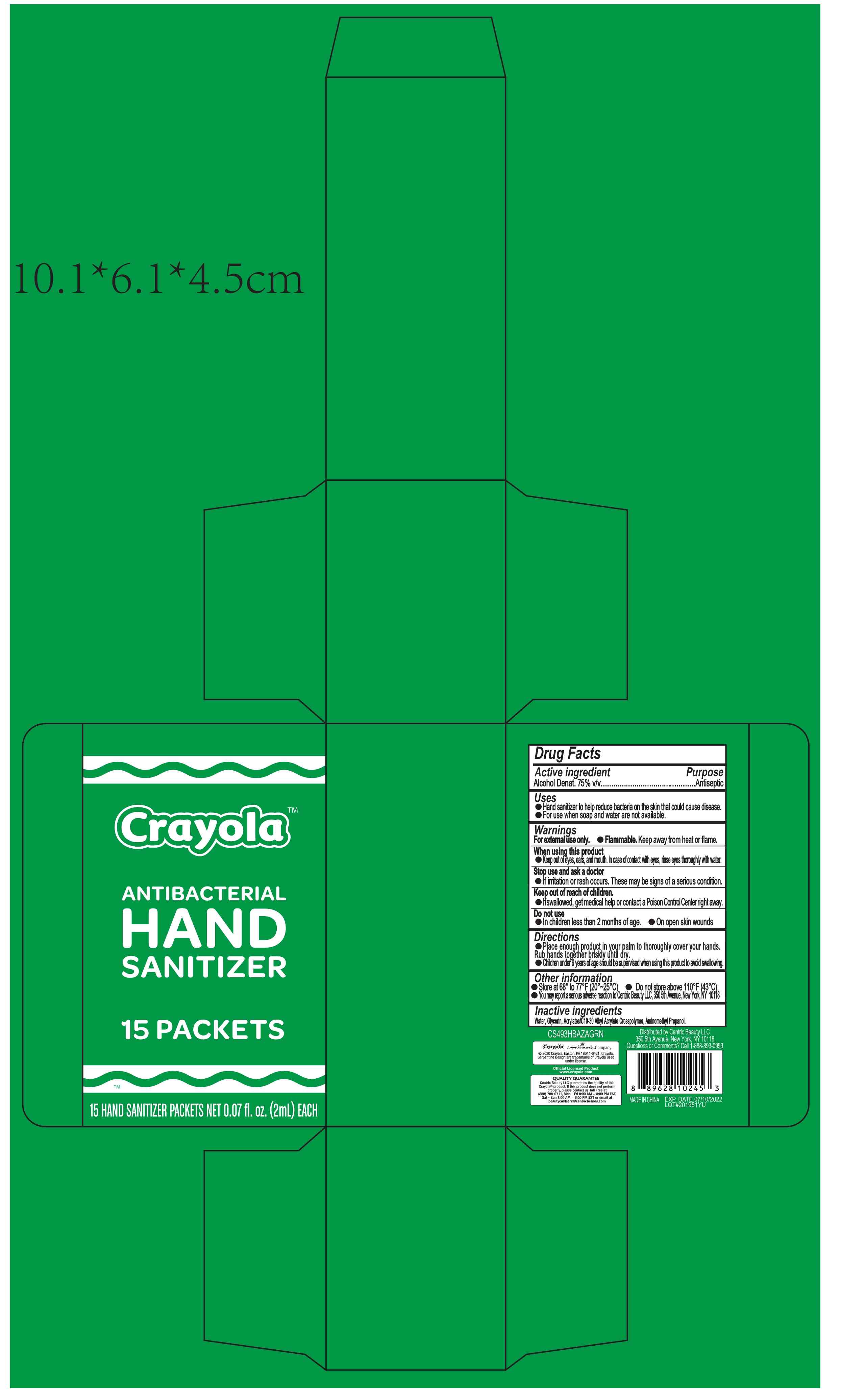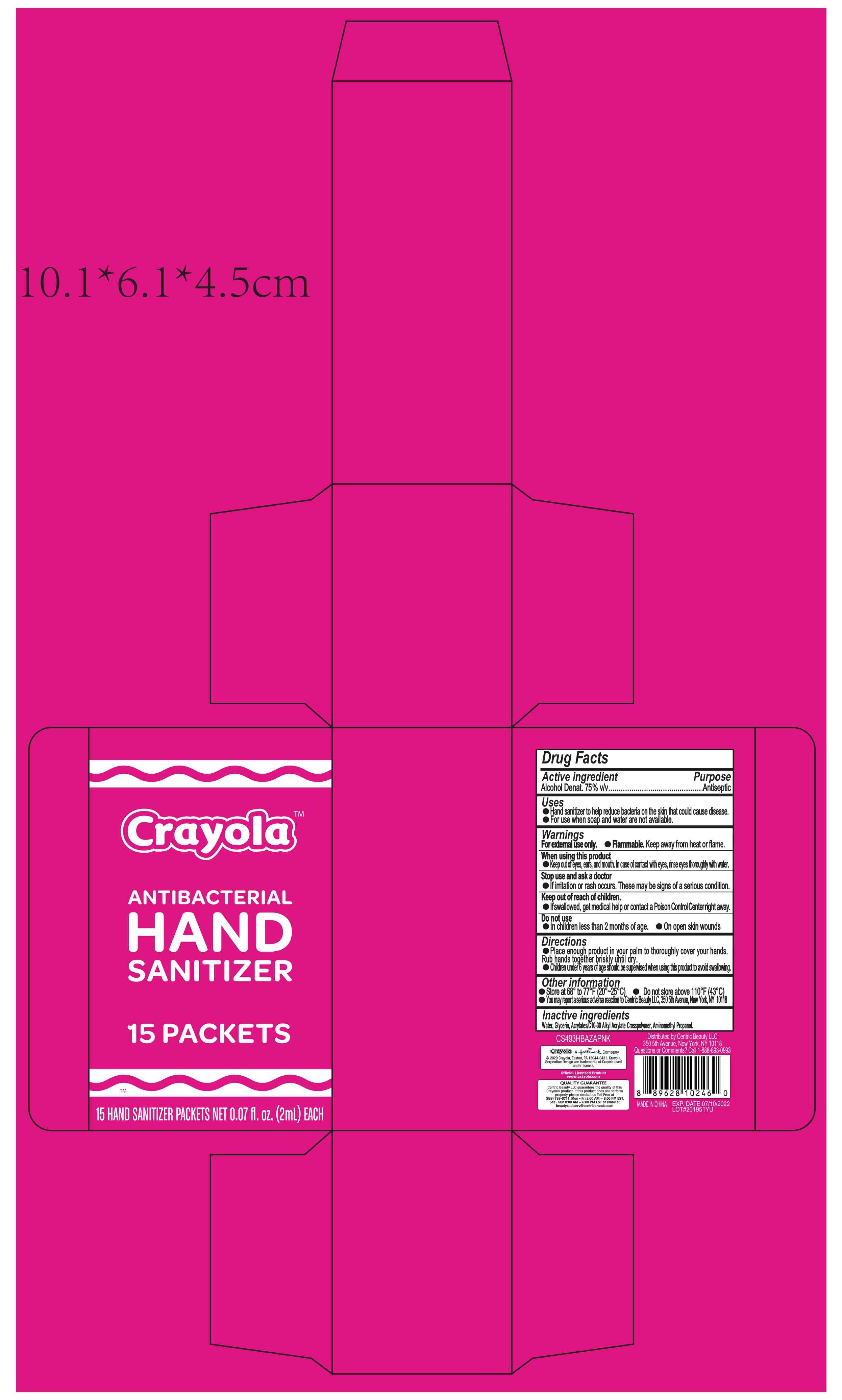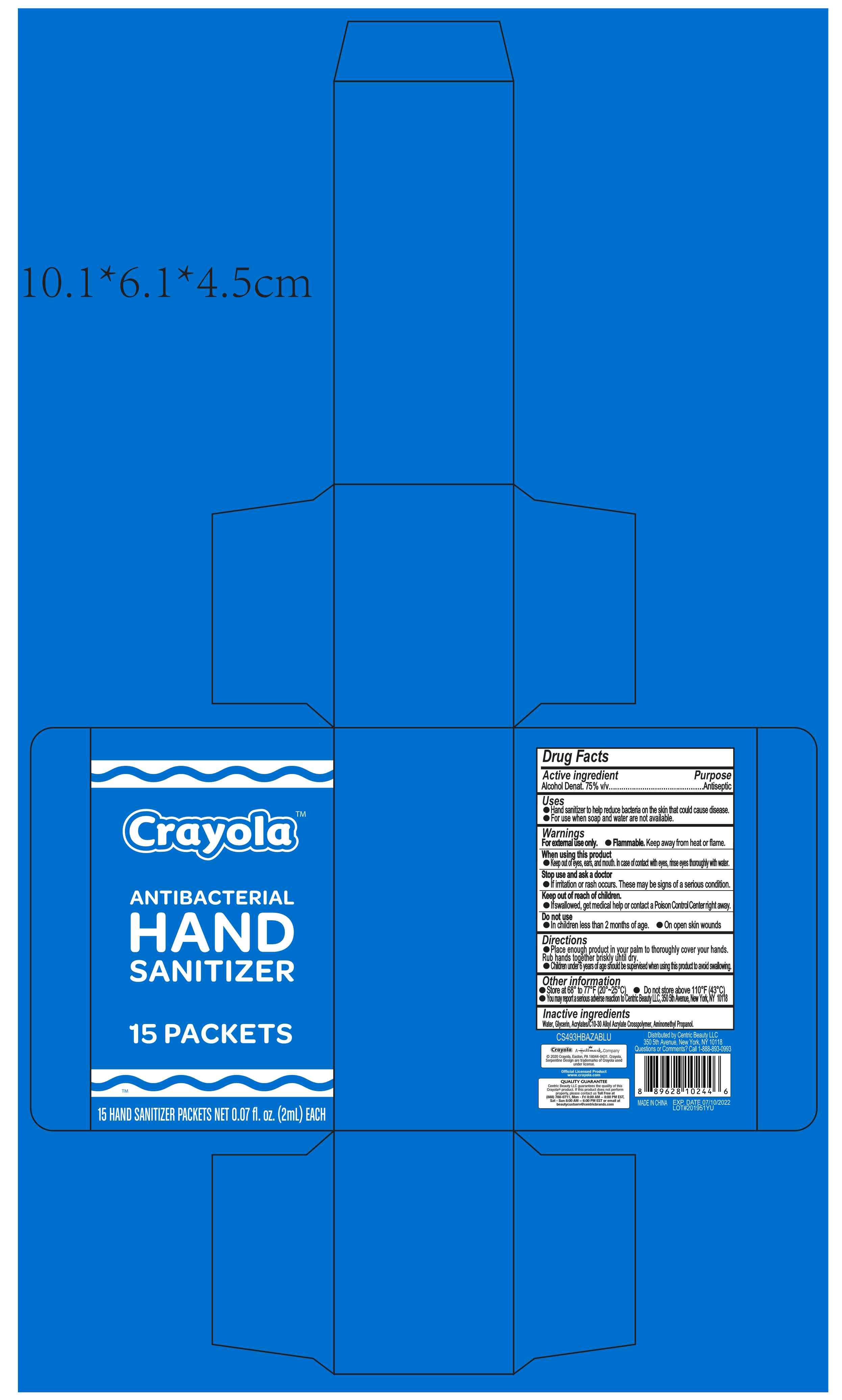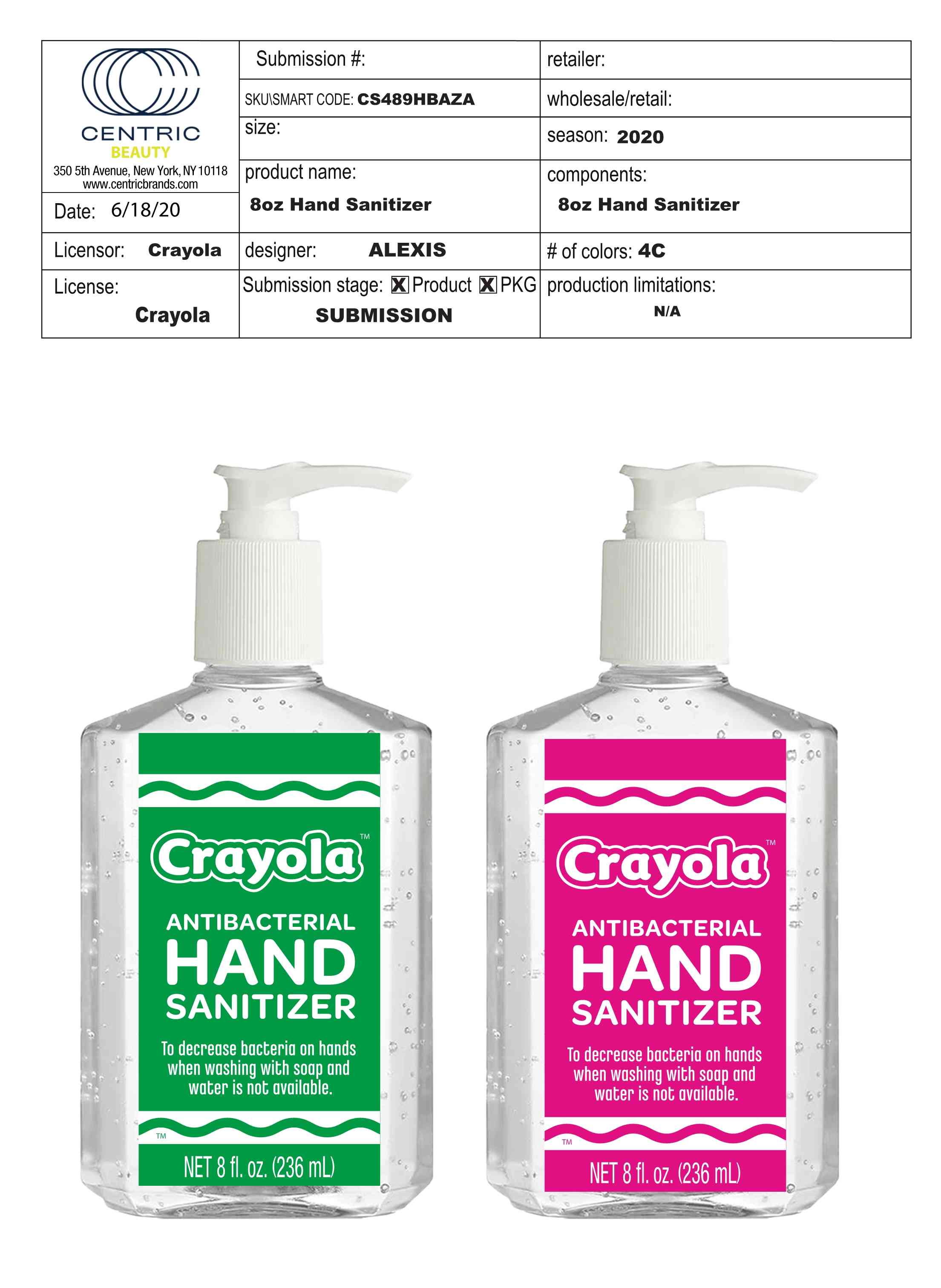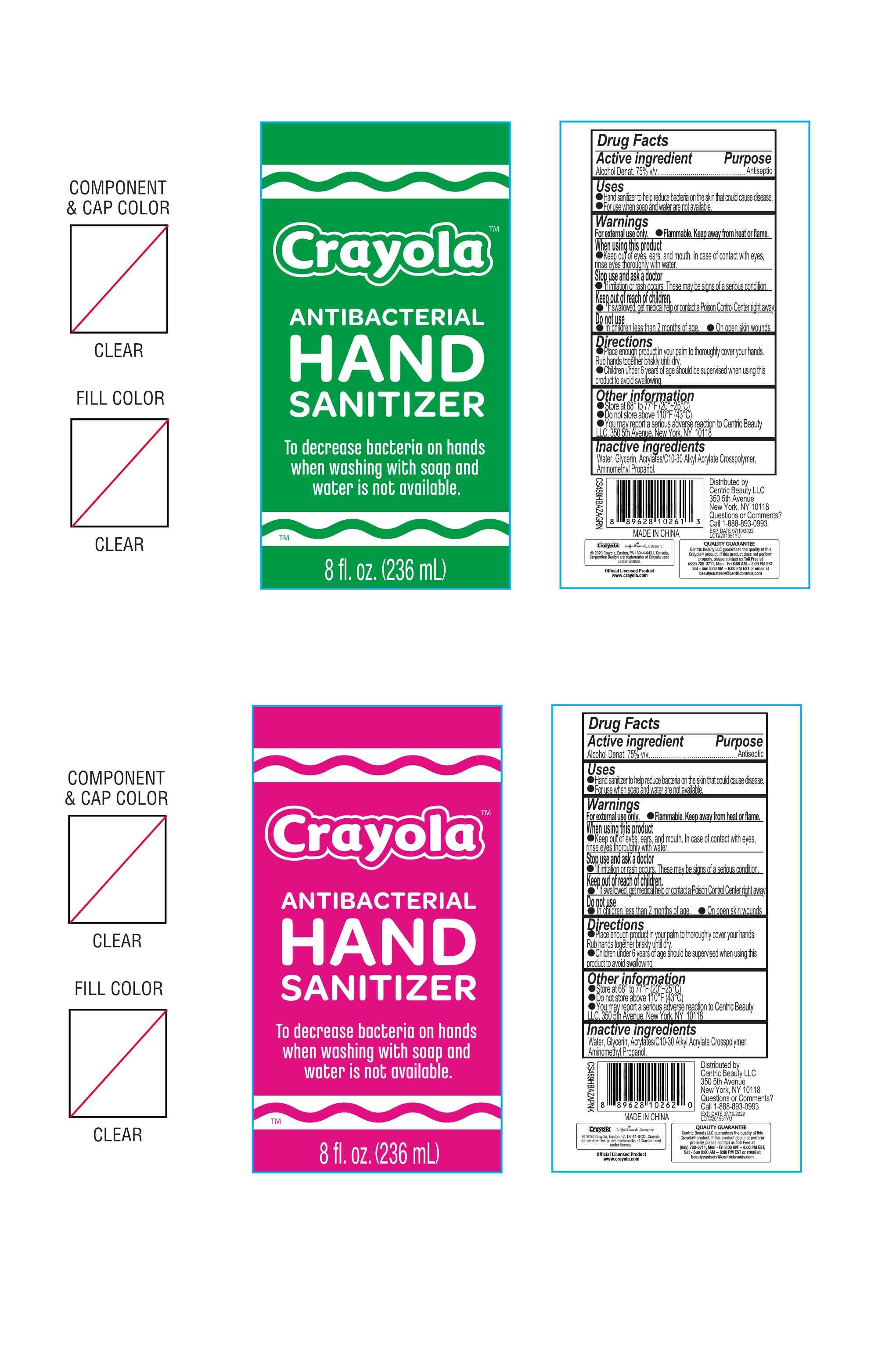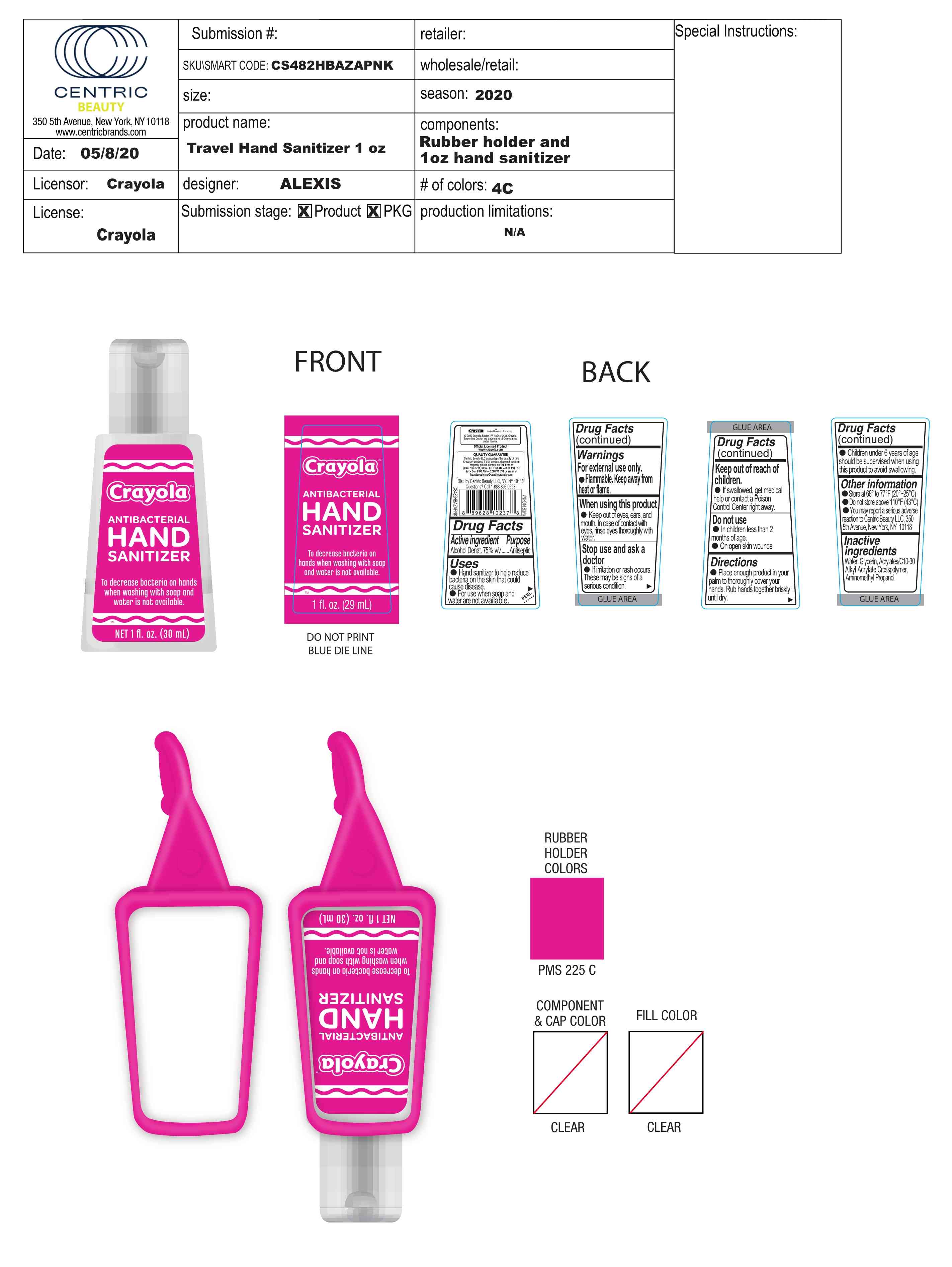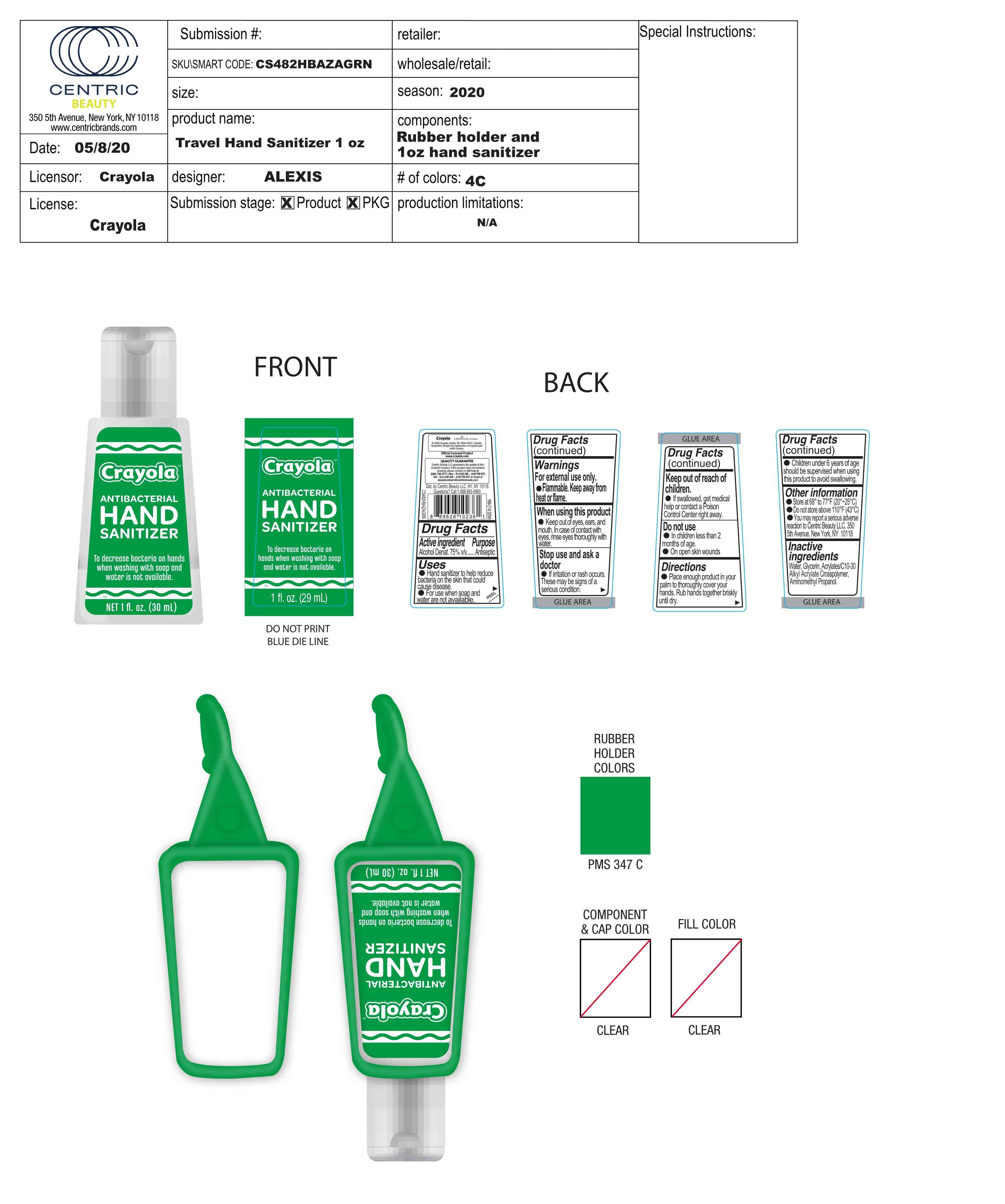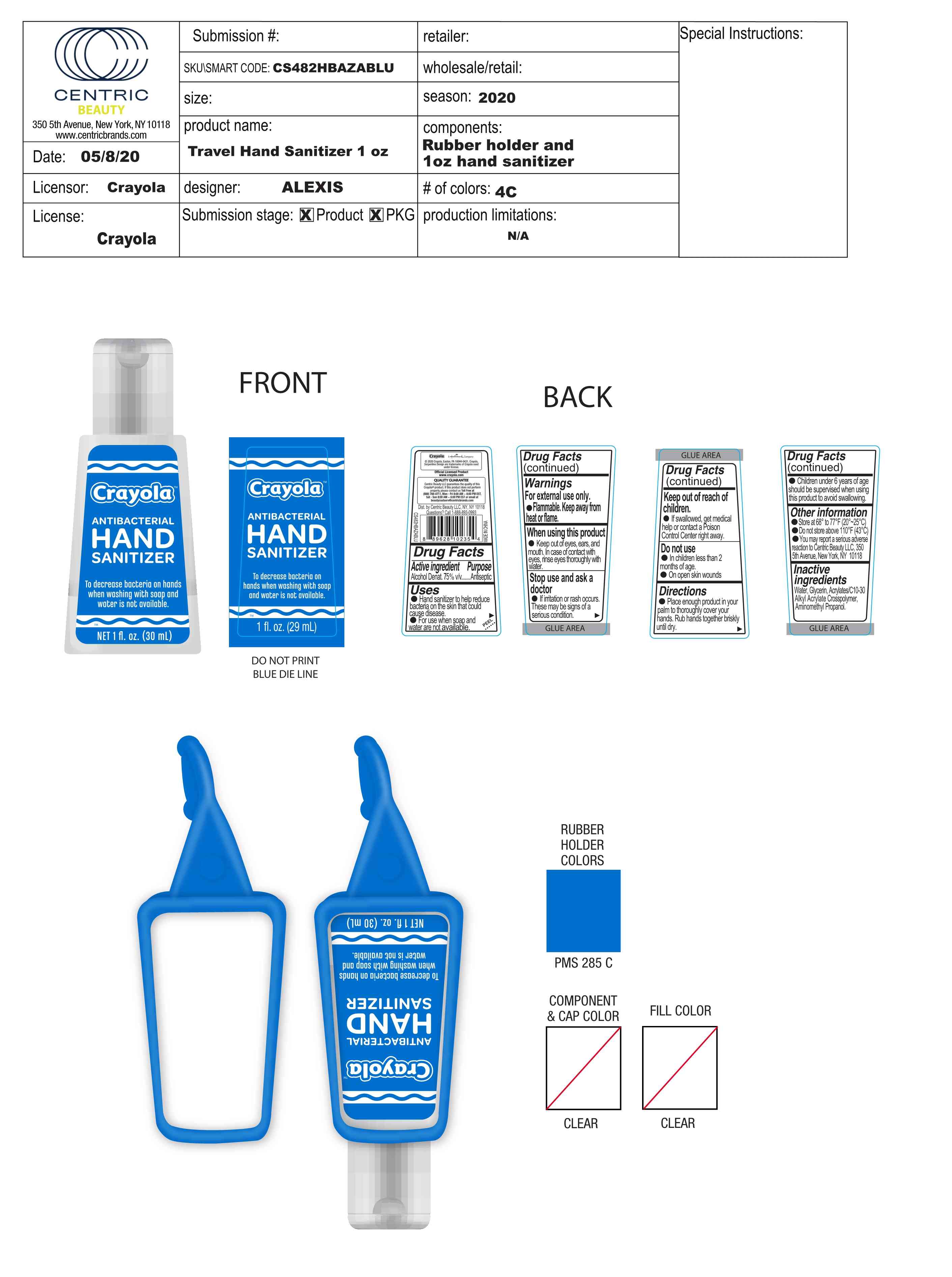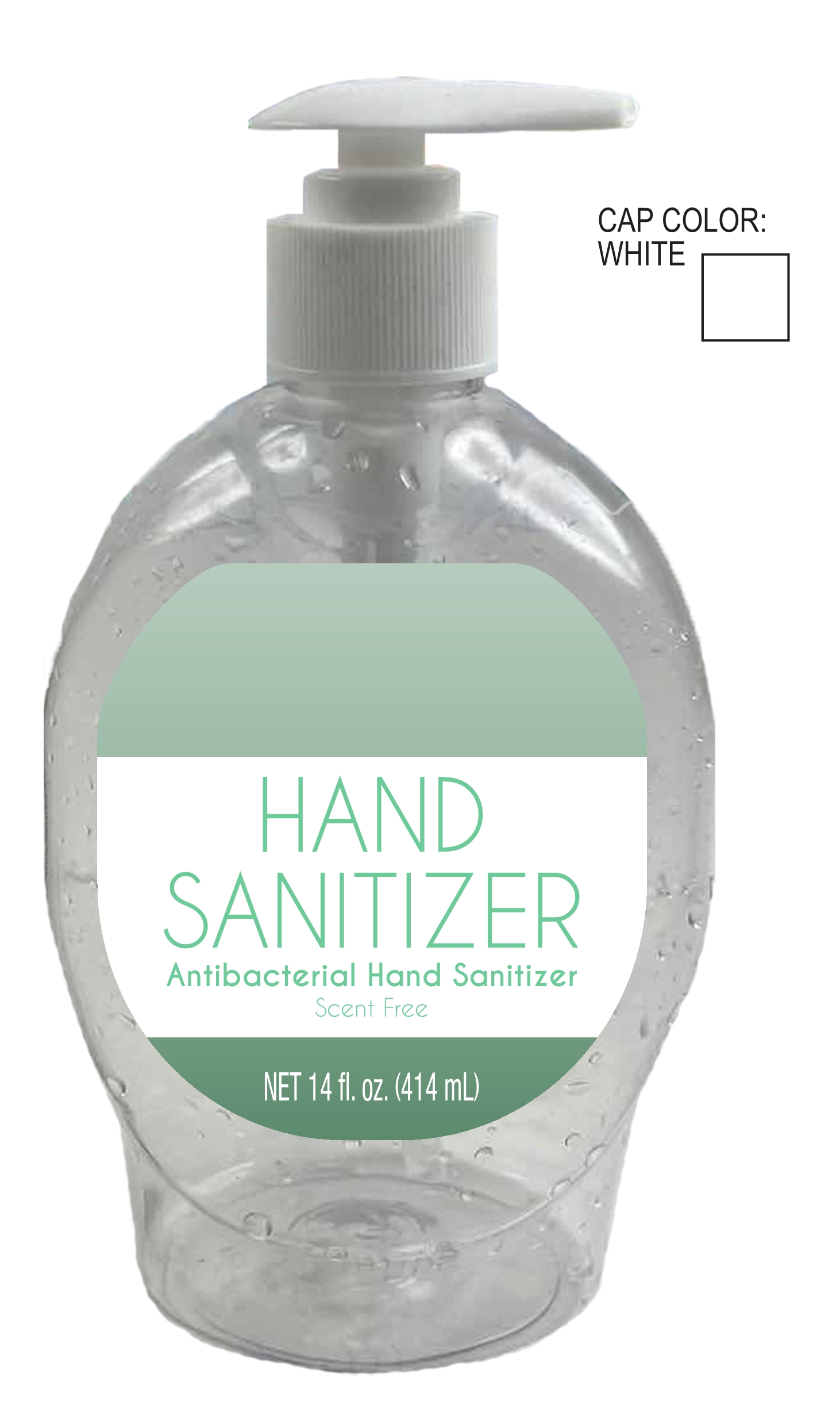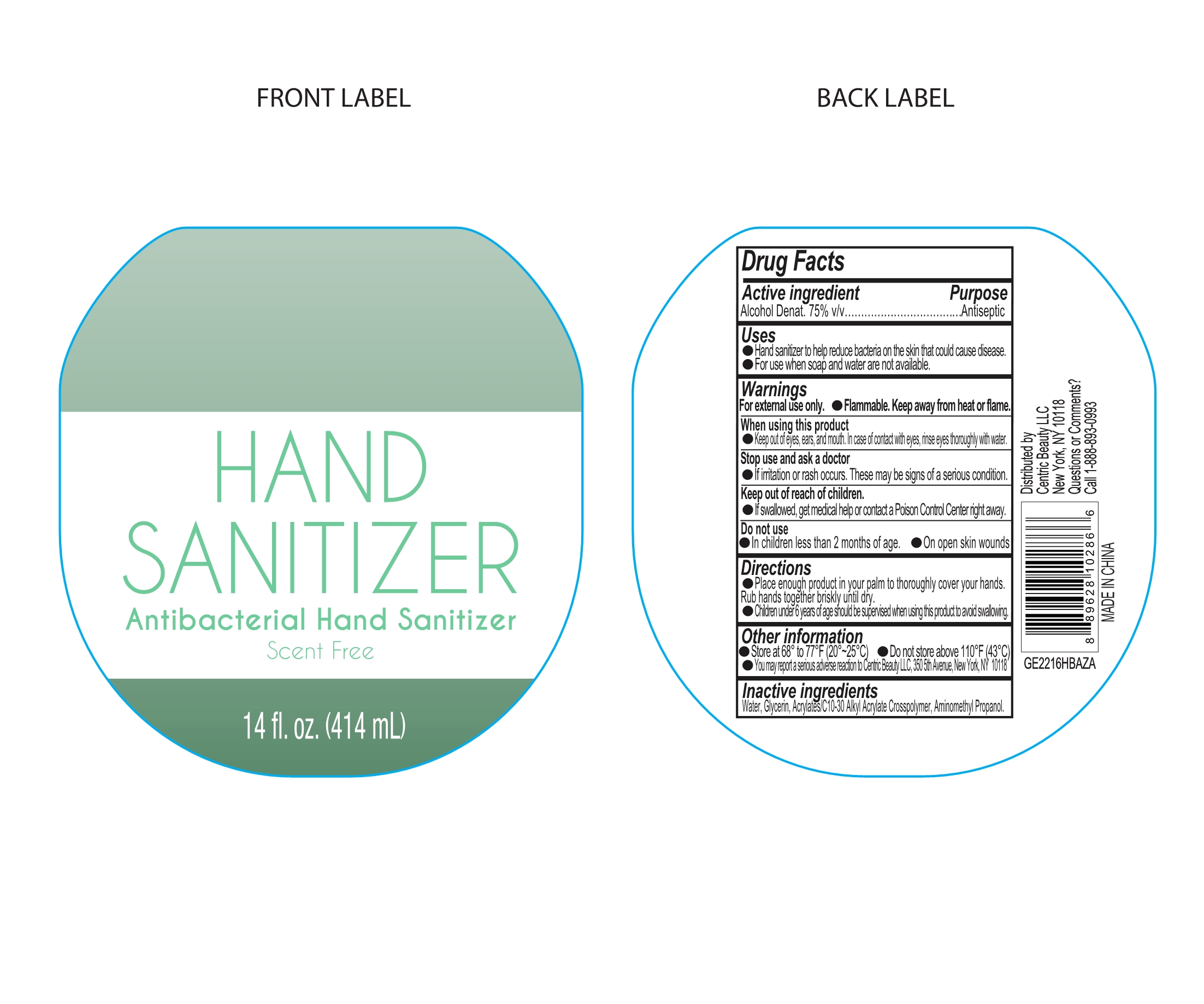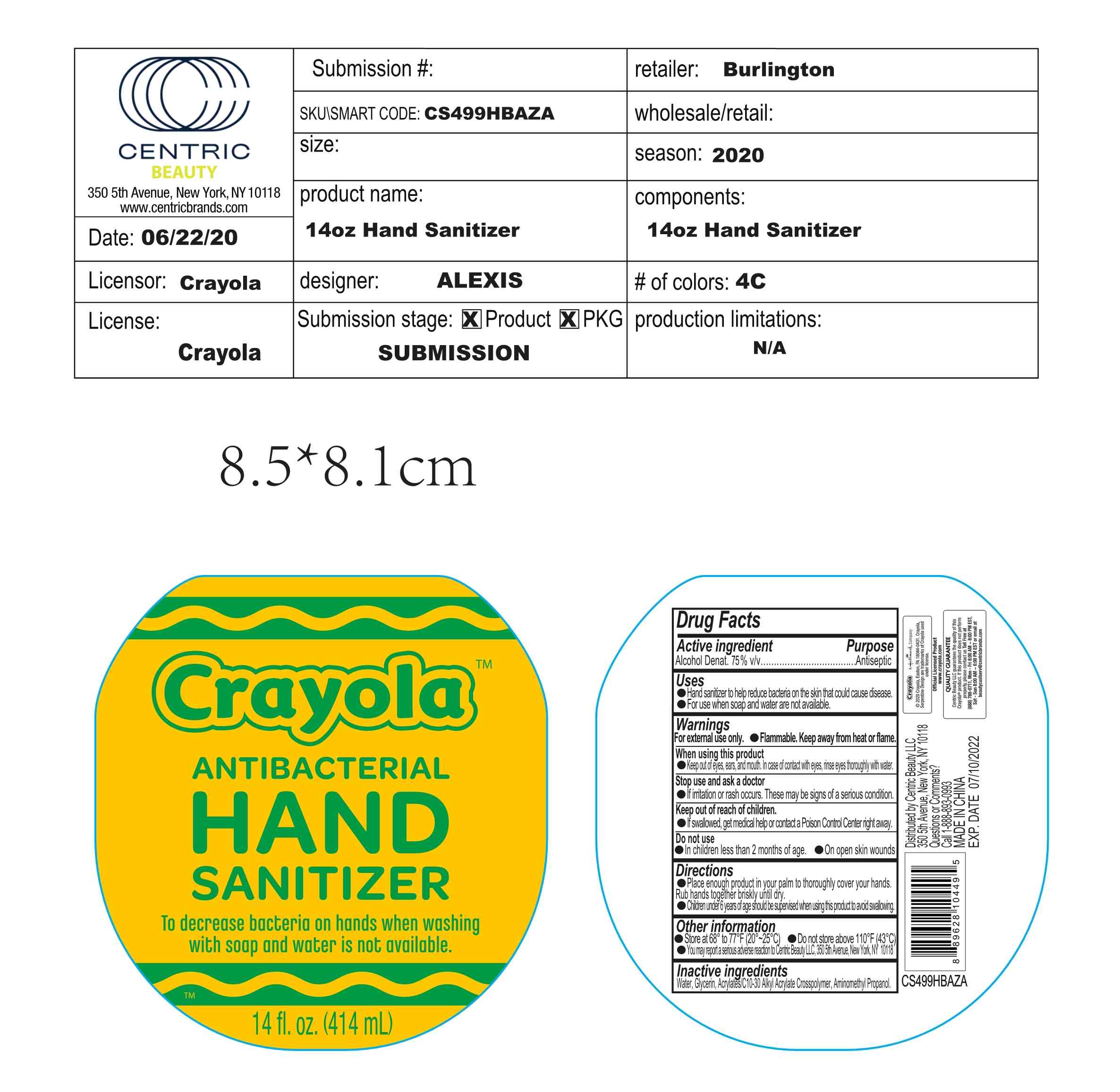 DRUG LABEL: Hand Sanitizer
NDC: 75427-012 | Form: GEL
Manufacturer: Jinhua City Wellmae Cosmetics Co., Ltd.
Category: otc | Type: HUMAN OTC DRUG LABEL
Date: 20220120

ACTIVE INGREDIENTS: ALCOHOL 75 mL/100 mL
INACTIVE INGREDIENTS: CARBOMER INTERPOLYMER TYPE A (55000 CPS); WATER; GLYCERIN; AMINOMETHYLPROPANOL

75427-012
Hand Sanitizer

ACTIVE INGREDIENT

Alcohol Denat.75% v/v

Purpose

Antiseptic

INDICATIONS AND USAGE

Hand sanitizer to help reduce bacteria on the skin that could cause disease.

For use when soap and water are not available.

WARNINGS

For external use only.
●Flammable. Keep away from heat or flame.

WHEN USING

Keep out of eyes, ears,and mouth, ln case of contact with eyes, rinse eyes thoroughly with water.

Do not use

● ln children less than 2 months of age.
● On open skin wounds

Stop use and ask a doctor

● lf swallowed, get medical help or contact a Poison Control Center right away.

Keep out of reach of children

If swallowed, get medical help or contact a Poison Control Center right away.

Directions

● Place enough product in your palm to thoroughly cover your hands. Rub hands together briskly until dry.
● Children under 6 years of age should be supervised when using this product to avoid swallowing.

Other Information

● Store at 68°to 77℉ (20°~25℃)
● Do not store above 110℉ (43℃)
● You may report a serious adverse reaction to Centric Beauty LLC, 3505th Avenue, New York, NY 10118

Inactive Ingredients

Water, Glycerin,Acrylates/c10-30 Alkyl Acrylate Crosspolymer, Aminomethyl Propand.